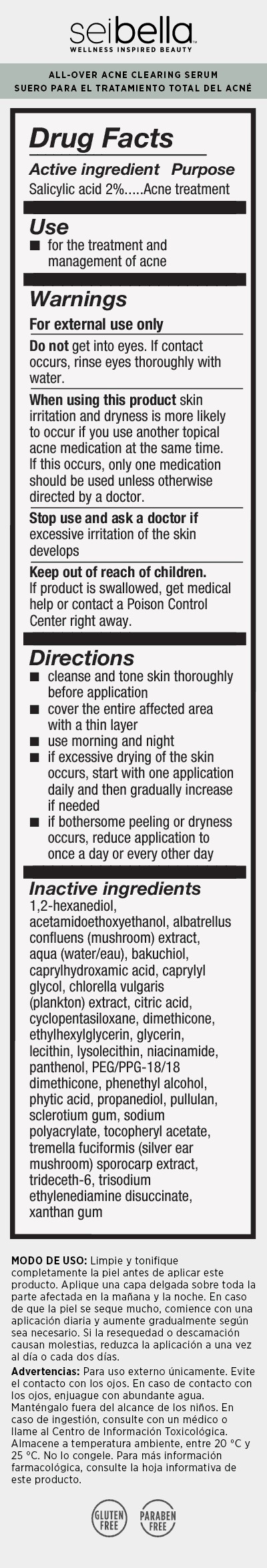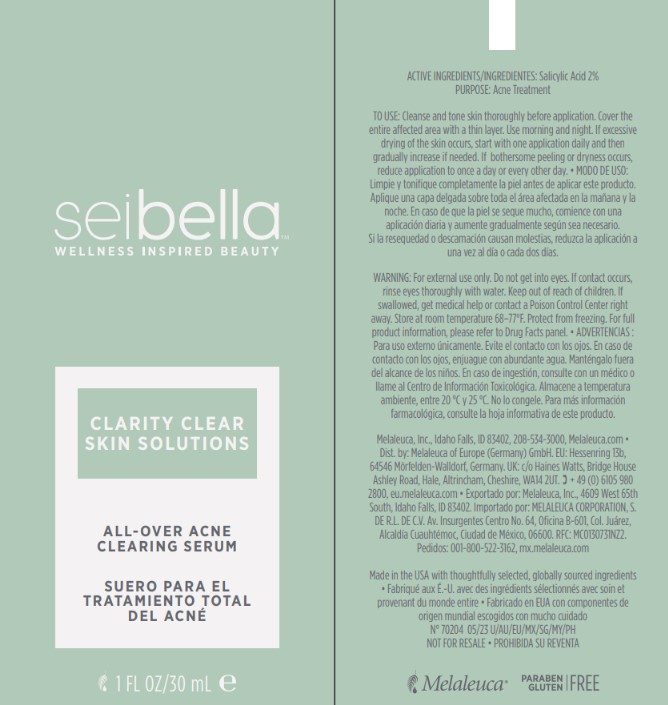 DRUG LABEL: Sei Bella Clarity Clear Acne All-Over Clearing Serum
NDC: 54473-400 | Form: SOAP
Manufacturer: Melaleuca, Inc.
Category: otc | Type: HUMAN OTC DRUG LABEL
Date: 20251231

ACTIVE INGREDIENTS: SALICYLIC ACID 0.6 g/30 mL
INACTIVE INGREDIENTS: 1,2-HEXANEDIOL; DIMETHICONE; TREMELLA FUCIFORMIS FRUITING BODY; CAPRYLYL GLYCOL; NIACINAMIDE; PULLULAN; BAKUCHIOL; XANTHAN GUM; PROPANEDIOL; PHENYLETHYL ALCOHOL; FYTIC ACID; TRISODIUM ETHYLENEDIAMINE DISUCCINATE; WATER; BETASIZOFIRAN; SODIUM POLYACRYLATE (2500000 MW); TRIDECETH-6; CHLORELLA VULGARIS; GLYCERIN; PANTHENOL; CYCLOMETHICONE 5; ETHYLHEXYLGLYCERIN; LYSOPHOSPHATIDYLCHOLINE, SOYBEAN; PEG/PPG-18/18 DIMETHICONE; .ALPHA.-TOCOPHEROL ACETATE; CAPRYLHYDROXAMIC ACID; ALBATRELLUS CONFLUENS FRUITING BODY; SOYBEAN LECITHIN; ACETAMIDOETHOXYETHANOL; CITRIC ACID MONOHYDRATE

Sei Bella Clarity Clear All-Over Acne Clearing Serum

Active Ingredient

Salicylic Acid 2%

Purpose

Acne Treatment

INDICATIONS AND USAGE

Use For the treatment and management of acne

Warnings

For external use only Do not get into eyes. If contact occurs, rinse eyes thoroughly with water.

When using this product skin irritation and dryness is more likely to occur if you use another topical acne medication at the same time. If this occurs, only one medication should be used unless otherwise directed by a doctor.

Stop use and ask a doctor ifexcessive irritation of the skin develops.

Keep out of reach of children. If this product is swallowed, get medical help or contact a Poison Control Center right away.

Directions

- Cleanse and tone skin thoroughly before application
- Cover the entire affected area with a thin layer
- Use morning and night
- If excessive drying of the skin occurs, start with one application daily and then gradually increase if needed
- If bothersome peeling or dryness occurs, reduce application to once a day or every other day

INACTIVE INGREDIENT

1,2 hexanediol, acetamidoethoxyethanol, albatrellus confluens (mushroom) extract, aqua (water/eau), bakuchiol, caprylhydroxamic acid, caprylyl glycol, chlorella vularis (plankton) extract, citric acid, cyclopentasiloxane, dimethicone, ethylhexylglycerin, glycerin, lecithin, lysolecithin, niacinamide, panthenol, PEG/PPG-18/18 dimethicone, phenethyl alcohol, phytic acid, propanediol, pullulan, sclerotium gum, sodium polyacrylate, tocopheryl acetate, tremella fuciformis (silver ear mushroom) sporocarp extract, trideceth-6, trisodium ethylenediamine disuccinate, xanthan gum